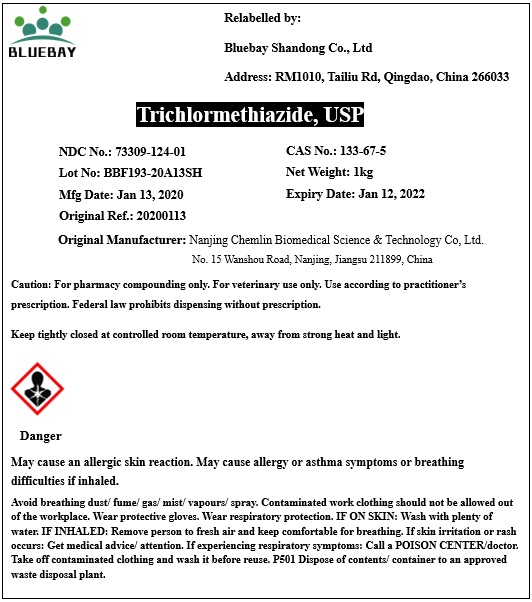 DRUG LABEL: Trichlormethiazide
NDC: 73309-124 | Form: POWDER
Manufacturer: BLUEBAY SHANDONG CO.,LTD
Category: other | Type: BULK INGREDIENT
Date: 20200416

ACTIVE INGREDIENTS: TRICHLORMETHIAZIDE 1 kg/1 kg

Trichlormethiazide